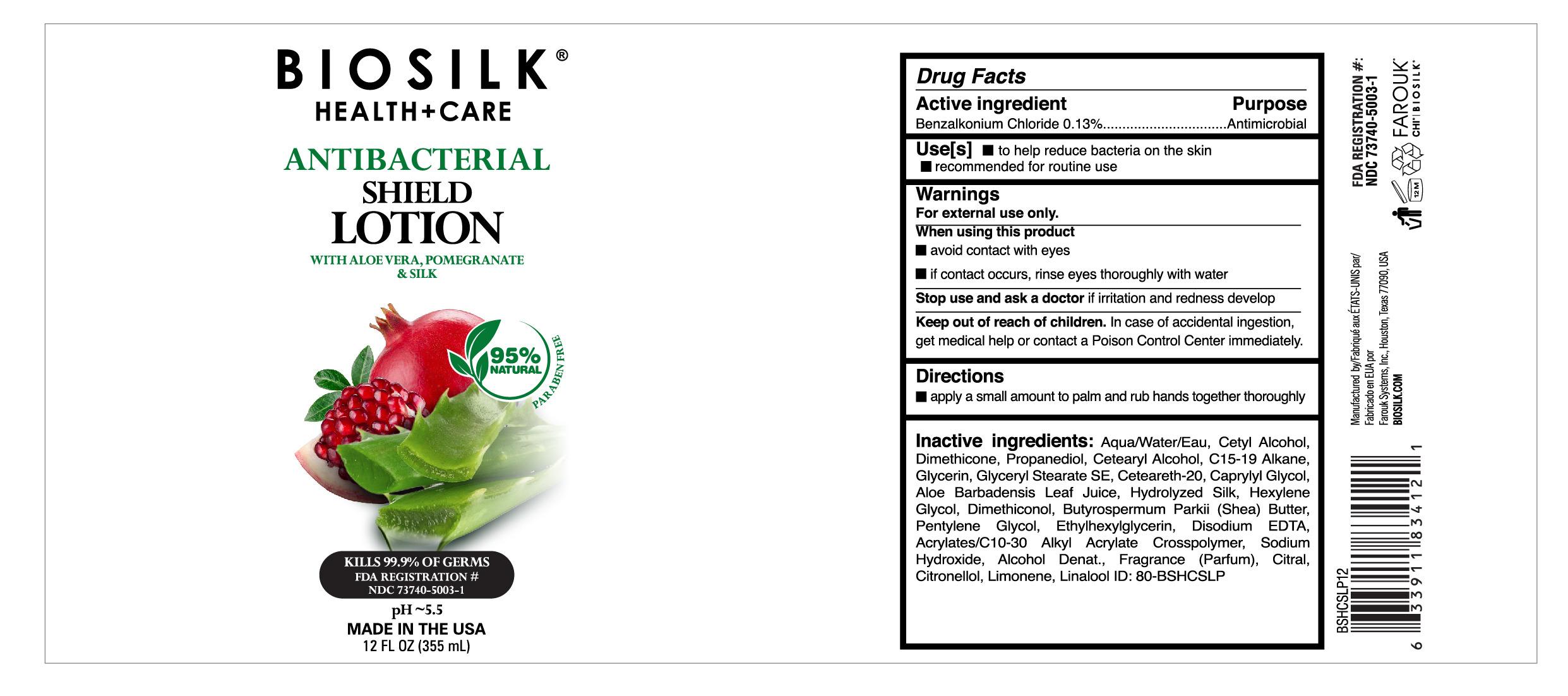 DRUG LABEL: Biosilk Pomegranite
NDC: 73740-5003 | Form: LOTION
Manufacturer: Farouk Systems, Inc.
Category: otc | Type: HUMAN OTC DRUG LABEL
Date: 20200824

ACTIVE INGREDIENTS: BENZALKONIUM CHLORIDE 0.13 g/100 g
INACTIVE INGREDIENTS: DIMETHICONE 1000 3.64 g/100 g; DIMETHICONOL (100000 CST) 0.36 g/100 g; EDETATE DISODIUM 0.15 g/100 g; SILK, ENZYME HYDROLYZED (1000 MW) 0.0011 g/100 g; GLYCERYL STEARATE SE 1.6 g/100 g; CAPRYLYL GLYCOL 1 g/100 g; FRAGRANCE CLEAN ORC0600327 0.23538 g/100 g; LIMONENE, (+)- 0.05139 g/100 g; ALCOHOL 0.013 g/100 g; HEXYLENE GLYCOL 0.4 g/100 g; BUTYROSPERMUM PARKII (SHEA) BUTTER UNSAPONIFIABLES 0.3 g/100 g; PENTYLENE GLYCOL 0.3 g/100 g; ETHYLHEXYLGLYCERIN 0.2 g/100 g; CARBOMER INTERPOLYMER TYPE A (55000 CPS) 0.1 g/100 g; CITRAL 0.00294 g/100 g; .BETA.-CITRONELLOL, (R)- 0.00588 g/100 g; C15-19 ALKANE 2 g/100 g; GLYCERIN 2 g/100 g; POLYOXYL 20 CETOSTEARYL ETHER 1.6 g/100 g; LINALOOL, (+/-)- 0.00441 g/100 g; PROPANEDIOL 2.1 g/100 g; CETOSTEARYL ALCOHOL 2 g/100 g; ALOE VERA LEAF 0.001 g/100 g; SODIUM HYDROXIDE 0.02 g/100 g; WATER 77.8849 g/100 g; CETYL ALCOHOL 3.9 g/100 g

Biosilk Health + Care Lotion with Pomegranite

Active Ingredient

Active ingredient Purpose
Benzalkonium Chloride 0.13%................................Antimicrobial

Warnings

Stop use and ask a doctor if irritation and redness develop

Warnings

Keep out of reach of children. In case of accidental ingestion,
get medical help or contact a Poison Control Center immediately.

Warnings

When using this product
avoid contact with eyes
if contact occurs, rinse eyes thoroughly with water

Warnings

For external use only.
When using this product
avoid contact with eyes
if contact occurs, rinse eyes thoroughly with water
Stop use and ask a doctor if irritation and redness develop
Keep out of reach of children. In case of accidental ingestion,
get medical help or contact a Poison Control Center immediately.

Inactive Ingredients

Inactive ingredients: Aqua/Water/Eau, Cetyl Alcohol,
Dimethicone, Propanediol, Cetearyl Alcohol, C15-19 Alkane,
Glycerin, Glyceryl Stearate SE, Ceteareth-20, Caprylyl Glycol,
Aloe Barbadensis Leaf Juice, Hydrolyzed Silk, Hexylene
Glycol, Dimethiconol, Butyrospermum Parkii (Shea) Butter,
Pentylene Glycol, Ethylhexylglycerin, Disodium EDTA,
Acrylates/C10-30 Alkyl Acrylate Crosspolymer, Sodium
Hydroxide, Alcohol Denat., Fragrance (Parfum), Citral,
Citronellol, Limonene, Linalool

Directions

apply a small amount to palm and rub hands together thoroughly

Use(s)

Use[s] to help reduce bacteria on the skin
recommended for routine use

Use(s)

Use[s] to help reduce bacteria on the skin

Biosilk

Health+Care

ANTIBACTERIAL
SHIELD
LOTION WITH ALOE VERA, POMEGRANATE

& SILK

95% Natural Paraben Free

KILLS 99.9% OF GERMS
FDA REGISTRATION #
NDC 73740-5003-1
PARABEN FREE
pH ~5.5

MADE IN THE USA

12 FL OZ (355 mL)